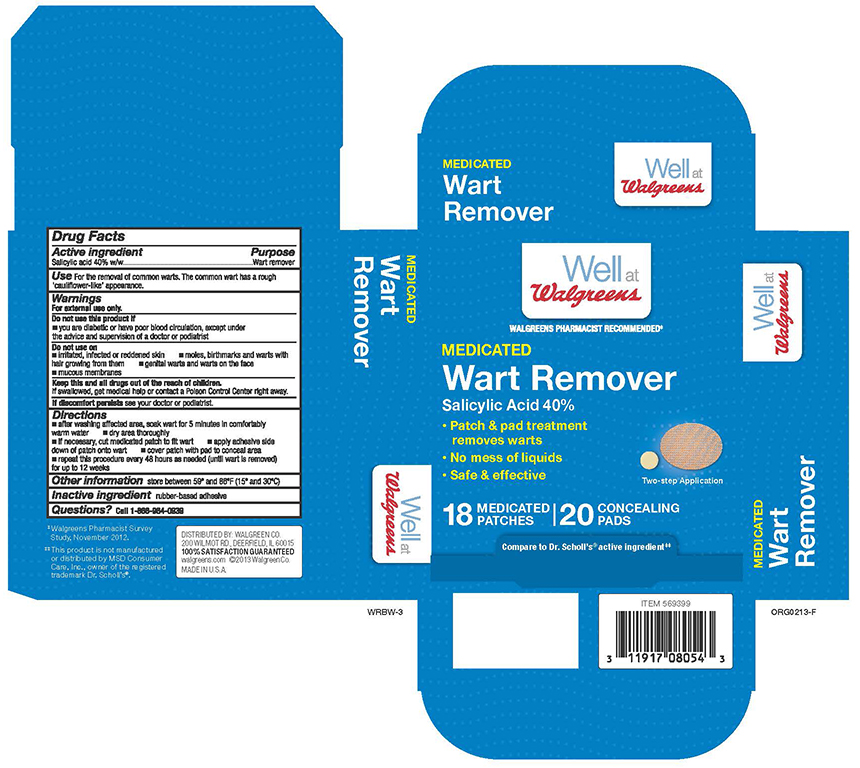 DRUG LABEL: Salicylic Acid
NDC: 0363-0203 | Form: PATCH
Manufacturer: Walgreen Company
Category: otc | Type: HUMAN OTC DRUG LABEL
Date: 20260120

ACTIVE INGREDIENTS: SALICYLIC ACID 40 mg/18 1
INACTIVE INGREDIENTS: HIGH DENSITY POLYETHYLENE; POLYVINYL ALCOHOL

Walgreens Wart Remover Patches

Active ingredient

Salicylic acid

Purpose

Wart remover

Use

for the removal of common warts. The common wart is easily recognized by the rough 'cauliflower-like' appearance.

Warnings

For external use only.

Do not use this product if

- you are a diabetic or have poor blood circulation, except under the advice and supervision of a doctor or podiatrist

Do not use on

- irritated, infected or reddened skin
- moles, birthmarks and warts with hair growing from them
- genital warts and warts on face
- mucous membranes

Keep out of reach of children

If swallowed, get medical help or contact a Poison Control Center right away.

Stop and ask a doctor

If discomfort persists see your doctor or podiatrist

Directions

- wash affected area, may soak wart in warm water for 5 minutes
- dry area thoroughly
- if necessary, cut medicated patch to fit wart
- apply adhesive side down of patch onto wart
- cover patch with pad to conceal area
- repeat this procedure every 48 hours as needed (until wart is removed) for up to 12 weeks

Other information

store between 59°F to 86°F (15°C to 30°C)

Inactive ingredients

rubber-based adhesive

Questions?

call 1-866-964-0939

Principal Display Panel

Well at Walgreens

MEDICATED

Wart Remover

Salicylic Acid 40%

- Patch & pad treatment removes warts
- No mess of liquids
- Safe & effective

18 MEDICATED PATCHES | 20 CONCEALING PADS